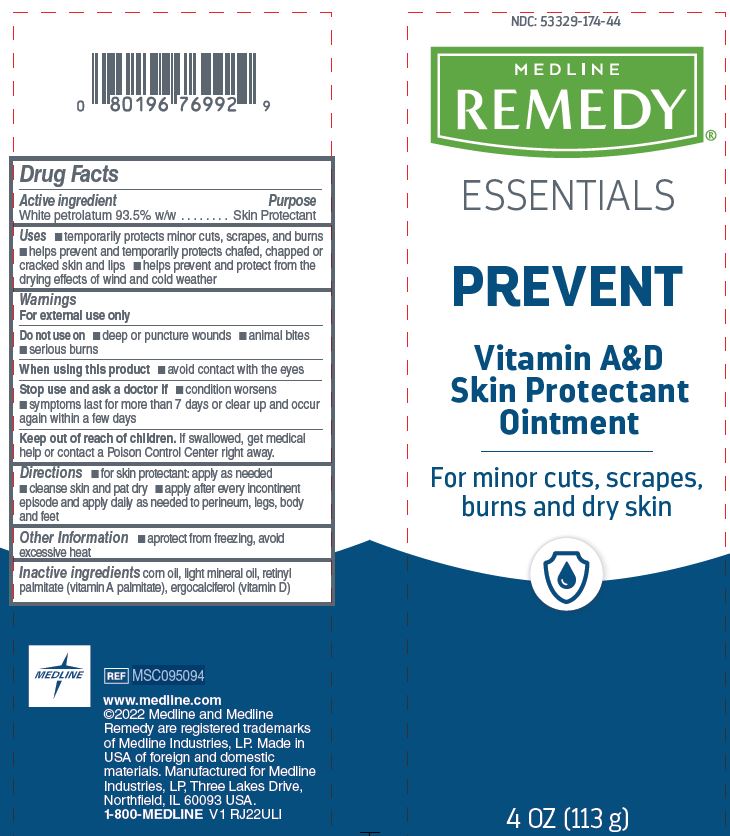 DRUG LABEL: Medline
NDC: 53329-174 | Form: OINTMENT
Manufacturer: Medline Industries, LP
Category: otc | Type: HUMAN OTC DRUG LABEL
Date: 20240508

ACTIVE INGREDIENTS: WHITE PETROLATUM 93.5 g/100 g
INACTIVE INGREDIENTS: VITAMIN D; LIGHT MINERAL OIL; CORN OIL; VITAMIN A PALMITATE

174 Remedy Essentials Vitamin A&D Ointment

Active ingredient

White petrolatum 93.5% w/w

Purpose

Skin protectant

Uses

- temporarily protects minor cuts, scrapes and burns
- helps prevent and temporarily protects chafed, chapped or cracked skin and lips
- helps prevent and protect from the drying effects of wind and cold weather

Warnings

For external use only.

Do not use on

- deep or puncture wounds
- animal bites
- serious burns

When using this product

- do not get into eyes

Stop use and ask a doctor if

- condition worsens
- symptoms last for more than 7 days or clear up and occur again within a few days

Keep out of reach of children.

In case of accidental ingestion, get medical help or contact a Poison Control Center right away.

Directions

- for skin protection: apply as needed
- cleanse skin and pat dry

Other information

- protect from freezing, avoid excessive heat

Inactive ingredients

lavender oil, light mineral oil, vitamin A palmitate (retinyl palmitate), vitamin D

Manufacturing Information

Manufactured for:

Medline Industries, LP

Three Lakes Drive, Northfield, IL 60093 USA

Made in USA of foreign and domestic materials

www.medline.com
1-800-MEDLINE (633-5463)

REF: MSC095094

V1 RJ22ULI